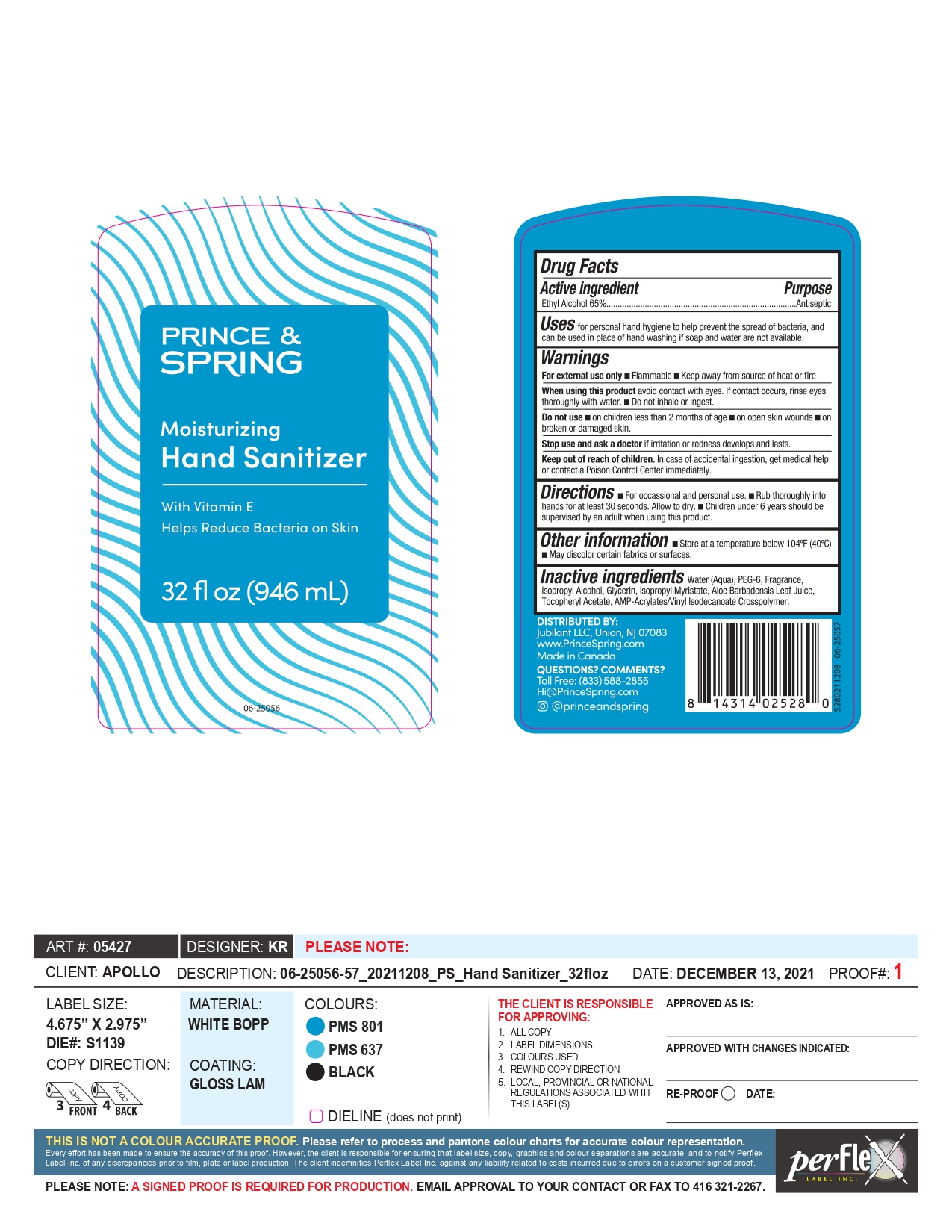 DRUG LABEL: Prince and Spring Moisturizing Hand Sanitizer
NDC: 63148-528 | Form: GEL
Manufacturer: Apollo Health and Beauty Care
Category: otc | Type: HUMAN OTC DRUG LABEL
Date: 20220104

ACTIVE INGREDIENTS: ALCOHOL 650 mg/1 mL
INACTIVE INGREDIENTS: WATER; POLYETHYLENE GLYCOL 300; ISOPROPYL ALCOHOL; GLYCERIN; ISOPROPYL MYRISTATE; ALOE VERA LEAF; .ALPHA.-TOCOPHEROL ACETATE, DL-; ACRYLATES/VINYL ISODECANOATE CROSSPOLYMER (10000 MPA.S NEUTRALIZED AT 0.5%); FRAGRANCE CLEAN ORC0600327

Prince and Spring Moisturizing Hand Sanitizer

Active Ingredients

Ethyl Alcohol (65%)

Purpose

Antiseptic

Uses

For personal hand hygiene to help prevent the spread of bacterial, and can be used in place of hand washing if soap and water are not available.

For external use only

- flammable
- keep away from source of heat or fire

When using this product

avoid contact with eyes. If contact occurs, rinse thoroughly with water. Do not inhale or ingest.

Do not use

- on children less than 2 months of age
- on open skin wounds
- on broken or damaged skin

Stop use and ask a doctor if

irritation or redness develops and lasts.

Keep out of reach of children.

In case of accidental ingestion, get medical help or contact a Poison Control Center immediately.

Directions

- For occasional and personal use
- Rub thoroughly into hands for at least 30 seconds. Allow to dry
- Children under 6 years should be supervised by an adult when using this product

Other Information

- store at a temperature below 104°F (40°C)
- may discolor certain fabrics or surfaces

Inactive Ingredients

Water, PEG-6, Fragrance, Isopropyl Alcohol, Glycerin, Isopropyl Myristate, Aloe Barbadensis Leaf Juice, Tocopheryl Acetate, AMP-Acrylates/Vinyl Isodecanoate Crosspolymer.